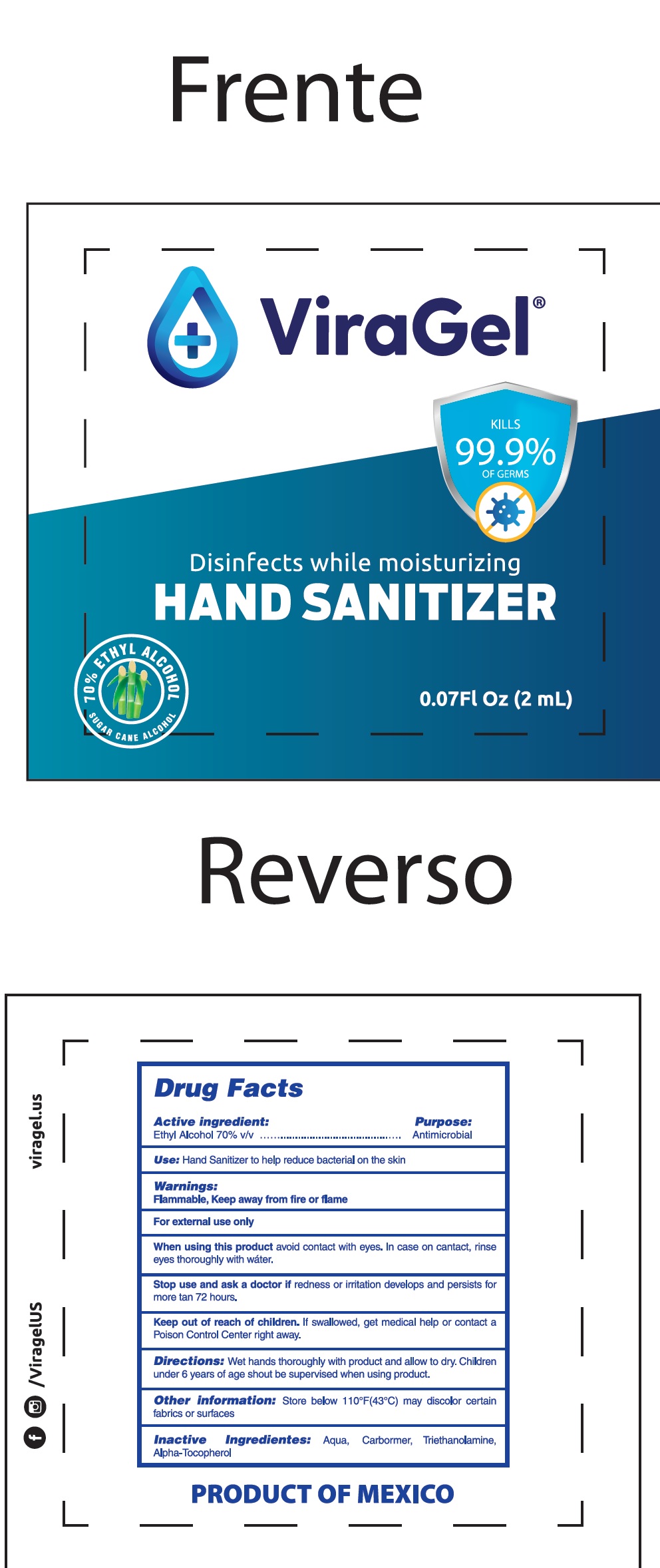 DRUG LABEL: Viragel Hand Sanitizer
NDC: 80007-001 | Form: GEL
Manufacturer: Comercial Emana, S.A. de C.V.
Category: otc | Type: HUMAN OTC DRUG LABEL
Date: 20200827

ACTIVE INGREDIENTS: ALCOHOL 0.7 mL/1 mL
INACTIVE INGREDIENTS: WATER; CARBOMER HOMOPOLYMER, UNSPECIFIED TYPE; TROLAMINE; .ALPHA.-TOCOPHEROL

Viragel Hand Sanitizer

Active ingredient:

Ethyl Alcohol 70% v/v

Purpose:

Antimicrobial

Use:

Hand sanitizer to help reduce bacteria on the skin

Warnings:

Flammable, Keep away from fire or flame.

For external use only.

When using this product

avoid contact with eyes. In case of contact , rinse eyes thoroughly with water.

Stop use and ask a doctor

if redness or irritation develops and persists for more than 72 hours.

Keep out of reach of children.

if swallowed, get medical help or contact a Poison Control Center right away.

Directions:

Wet hands thoroughly with product and allow to dry. Children under 6 years of age should be supervised when using this product.

Other information:

Store below 110°F (43°C) may discolor certain fabrics or surfaces

Inactive Ingredients:

Aqua, Carbomer, Triethanolamine, Alpha-Tocopherol